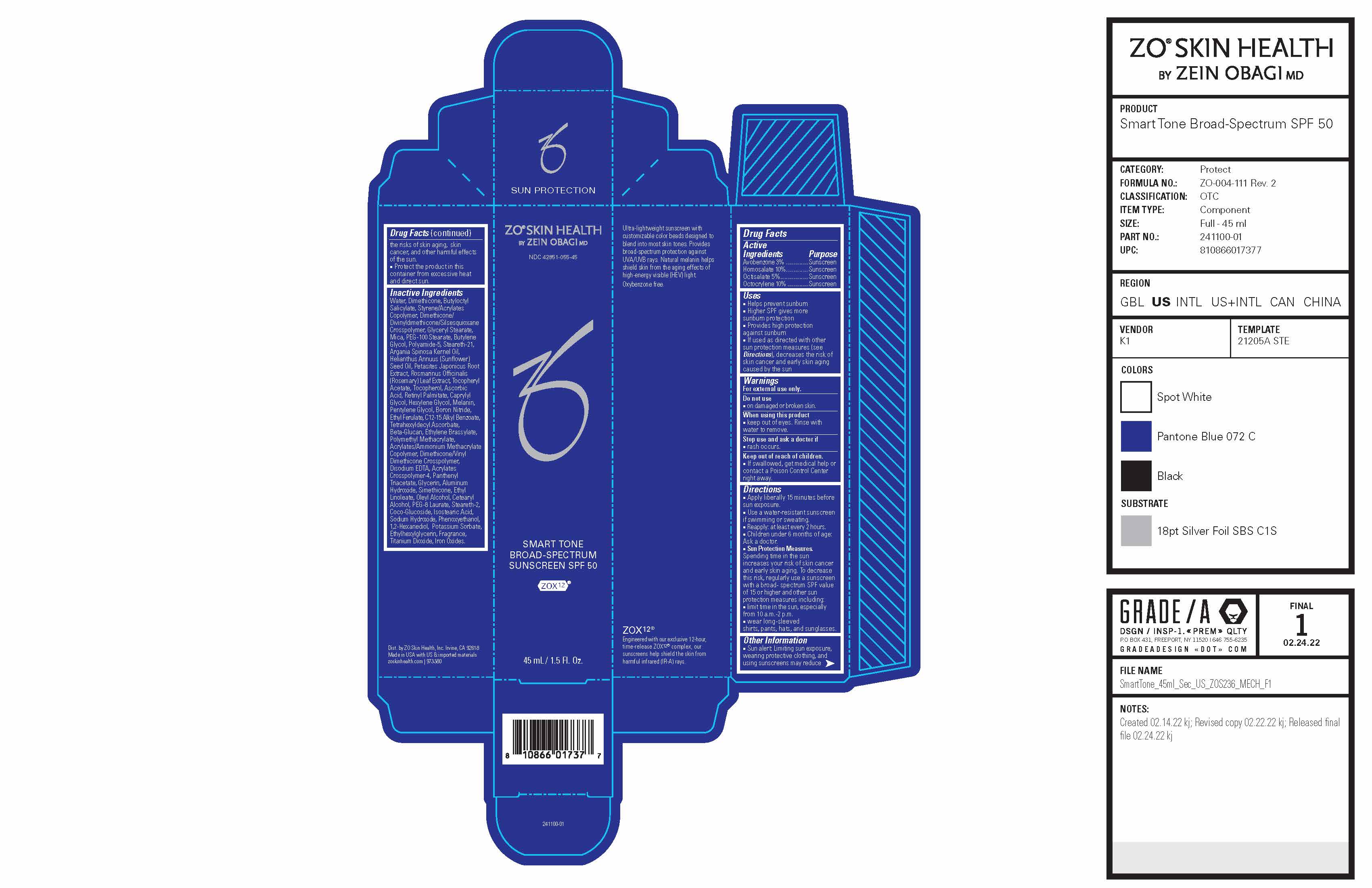 DRUG LABEL: ZO Skin Health Smart Tone Broad-Spectrum Sunscreen SPF 50
NDC: 42851-055 | Form: LOTION
Manufacturer: ZO Skin Health, Inc.
Category: otc | Type: HUMAN OTC DRUG LABEL
Date: 20241101

ACTIVE INGREDIENTS: OCTOCRYLENE 100 mg/1 mL; AVOBENZONE 30 mg/1 mL; HOMOSALATE 100 mg/1 mL; OCTISALATE 50 mg/1 mL
INACTIVE INGREDIENTS: GLYCERYL MONOSTEARATE; BUTYLOCTYL SALICYLATE; CAPRYLYL GLYCOL; BUTYLENE GLYCOL; ETHYL FERULATE; TETRAHEXYLDECYL ASCORBATE; EDETATE DISODIUM ANHYDROUS; STEARETH-21; SUNFLOWER OIL; PETASITES JAPONICUS ROOT; PENTYLENE GLYCOL; ALKYL (C12-15) BENZOATE; HEXYLENE GLYCOL; BORON NITRIDE; DIMETHICONE/DIVINYLDIMETHICONE/SILSESQUIOXANE CROSSPOLYMER; MICA; ROSEMARY; ALPHA-TOCOPHEROL ACETATE; TOCOPHEROL; ASCORBIC ACID; VITAMIN A PALMITATE; ETHYLENE BRASSYLATE; POLY(METHYL METHACRYLATE; 450000 MW); DIMETHICONE/VINYL DIMETHICONE CROSSPOLYMER (SOFT PARTICLE); COCO GLUCOSIDE; PHENOXYETHANOL; POTASSIUM SORBATE; ARGAN OIL; ALUMINUM HYDROXIDE; OLEYL ALCOHOL; ALCOHOL; STEARETH-2; SODIUM HYDROXIDE; ETHYLHEXYLGLYCERIN; FERRIC OXIDE RED; WATER; GLYCERIN; PANTHENOL TRIACETATE, (+)-; DIMETHICONE; PEG-100 STEARATE; ETHYL LINOLEATE; PEG-8 LAURATE; ISOSTEARIC ACID; 1,2-HEXANEDIOL; TITANIUM DIOXIDE

ZO® Skin Health Smart Tone Broad-Spectrum Sunscreen SPF 50
National Drug Codes 42851-055-45, 42851-055-20

Drug Facts

Active Ingredients

Active Ingredients | Purpose
Avobenzone 3% ............... | Sunscreen
Homosalate 10%............... | Sunscreen
Octisalate 5%................... | Sunscreen
Octocrylene 10% .............. | Sunscreen

Uses

- Helps prevent sunburn
- Higher SPF gives more sunburn protection
- Provides high protection against sunburn
- If used as directed with other sun protection measures (see Directions), decreases the risk of skin cancer and early skin aging caused by the sun

Warnings

For external use only.

Do not use

- on damaged or broken skin.

When using this product

- keep out of eyes. Rinse with water to remove.

Stop use and ask a doctor if

- rash occurs.

Keep out of reach of children.

- If swallowed, get medical help or contact a Poison Control Center right away.

Directions

- Apply liberally 15 minutes before sun exposure.
- Use a water-resistant sunscreen if swimming or sweating.
- Reapply: at least every 2 hours.
- Children under 6 months of age: Ask a doctor.
- Sun Protection Measures.Spending time in the sun increases your risk of skin cancer and early skin aging. To decrease this risk, regularly use a sunscreen with a broad- spectrum SPF value of 15 or higher and other sun
  protection measures including: ■ limit time in the sun, especially from 10 a.m.-2 p.m. ■ wear long-sleeved shirts, pants, hats, and sunglasses.

Other Information

- Protect the product in this container from excessive heat and direct sun.

Inactive Ingredients

Water, Dimethicone, Butyloctyl Salicylate, Styrene/Acrylates Copolymer, Dimethicone/Divinyldimethicone/Silsesquioxane Crosspolymer, Glyceryl Stearate, Mica, PEG-100 Stearate, Butylene Glycol, Polyamide-5, Steareth-21, Argania Spinosa Kernel Oil, Helianthus Annuus (Sunflower) Seed Oil, Petasites Japonicus Root Extract, Rosmarinus Officinalis (Rosemary) Leaf Extract, Tocopheryl Acetate, Tocopherol, Ascorbic Acid, Retinyl Palmitate, Caprylyl Glycol, Hexylene Glycol, Melanin, Pentylene Glycol, Boron Nitride, Ethyl Ferulate, C12-15 Alkyl Benzoate, Tetrahexyldecyl Ascorbate, Beta-Glucan, Ethylene Brassylate, Polymethyl
Methacrylate, Acrylates/Ammonium Methacrylate Copolymer, Dimethicone/Vinyl Dimethicone Crosspolymer, Disodium EDTA, Acrylates Crosspolymer-4, Panthenyl Triacetate, Glycerin, Aluminum Hydroxide, Simethicone, Ethyl Linoleate, Oleyl Alcohol,
Cetearyl Alcohol, PEG-8 Laurate, Steareth-2, Coco-Glucoside, Isostearic Acid, Sodium Hydroxide, Phenoxyethanol, 1,2-Hexanediol, Potassium Sorbate, Ethylhexylglycerin, Fragrance, Titanium Dioxide, Iron Oxides.

RECENT MAJOR CHANGES

Updated Directions section’s classification from Other Safety Information to Indications & Usage.

Designated the Drug Facts parent with classification of Dosage & Administration. Preceding transmission was accepted without a category.

Principal Display Panel

ZO® SKIN HEALTH

by ZEIN OBAGI MD

NDC 42851-055-45

Smart Tone Broad-Spectrum Sunscreen SPF 50

ZOX12®

Ultra-lightweight sunscreen with customizable color beads designed to blend into most skin tones. Provides broad-spectrum protection against UVA/UVB rays. Natural melanin helps shield skin from the aging effects of high-energy visible (HEV) light. Oxybenzone free.

ZOX12®

Engineered with our exclusive 12-hour, time-release ZOX12®complex, our sunscreens help shield the skin from harmful infrared (IR-A) rays.

Dist. by ZO Skin Health, Inc. Irvine, CA 92618
Made in USA with US & imported materials
zoskinhealth.com | 973380